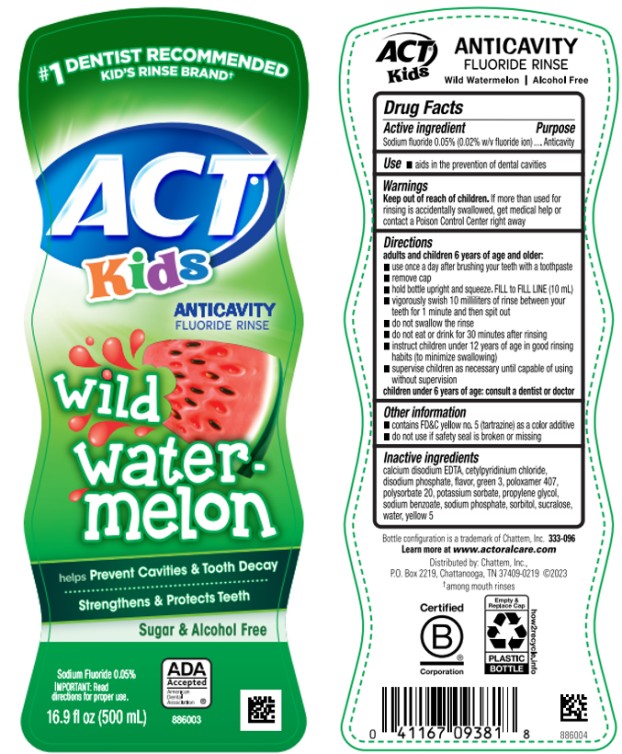 DRUG LABEL: ACT Kids Anticavity Fluoride
NDC: 41167-0938 | Form: RINSE
Manufacturer: Chattem, Inc.
Category: otc | Type: HUMAN OTC DRUG LABEL
Date: 20241016

ACTIVE INGREDIENTS: SODIUM FLUORIDE 0.5 mg/1 mL
INACTIVE INGREDIENTS: EDETATE CALCIUM DISODIUM ANHYDROUS; CETYLPYRIDINIUM CHLORIDE; SODIUM PHOSPHATE, DIBASIC, ANHYDROUS; FD&C GREEN NO. 3; POLOXAMER 407; POLYSORBATE 20; POTASSIUM SORBATE; PROPYLENE GLYCOL; SODIUM BENZOATE; SODIUM PHOSPHATE; SORBITOL; SUCRALOSE; WATER; FD&C YELLOW NO. 5

ACT Kids Anticavity Fluoride Rinse Watermelon

ACT® Anticavity Wild Watermelon

Fluoride Rinse

Active ingredient

Sodium Fluoride 0.05% (0.02% w/v fluoride ion)

Purpose

Anticavity

Use

- aids in the prevention of dental cavities

Warnings

Keep out of reach of children.

If more than used for rinsing is accidently swallowed, get medical help or contact Poison Control Center right away.

Directions

adults and children 6 years of age and older:

- use once a day after brushing your teeth with a toothpaste
- remove cap
- hold bottle upright and squeeze. Fill to FILL LINE (10 mL)
- vigorously swish 10 milliliters of rinse between your teeth for 1 minute and then spit out
- do not swallow the rinse
- do not eat or drink for 30 minutes after rinsing
- instruct children under 12 years of age in good rinsing habits (to minimize swallowing)
- supervise children as necessary until capable of using without supervision

children under 6 years of age: consult a dentist or doctor.

Other Information

- contains FD&C yellow no.5 (tartrazine) as a color additive
- do not use if safety seal is broken or missing

Inactive ingredients

calcium disodium EDTA, cetylpyridinium chloride, disodium phosphate, flavor, green 3, poloxamer 407, polysorbate 20, potassium sorbate, propylene glycol, sodium benzoate, sodium phosphate, sorbitol, sucralose, water, yellow 5 (309-023)

Principal Display Panel

ACT
Kids
ANTICAVITY
FLUROIDE RINSE
Wild Watermelon
Sugar & Alcohol Free
Sodium Fluoride 0.05%
16.9 fl oz (500 mL)